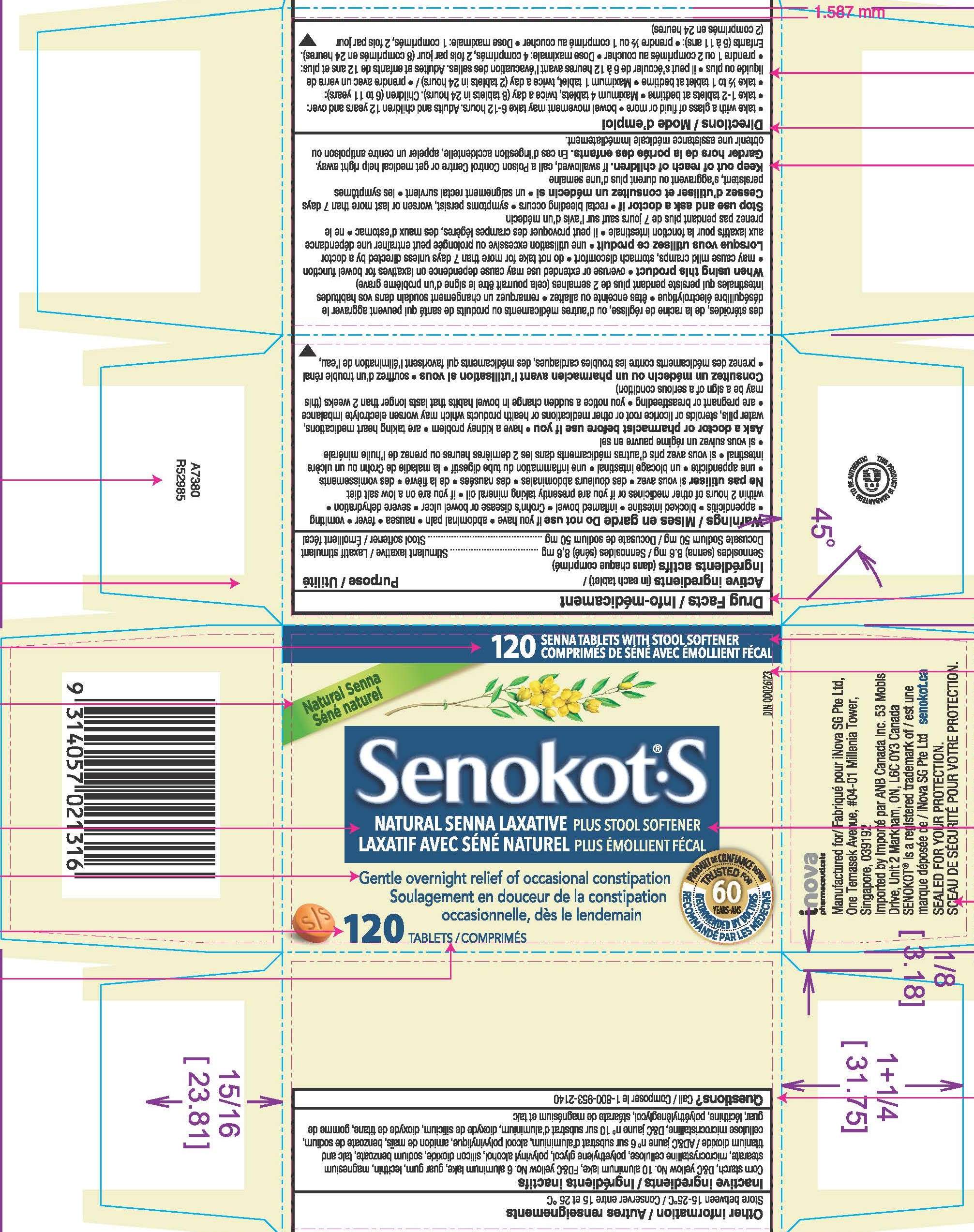 DRUG LABEL: Sennosides, Docusate Sodium
NDC: 10267-5609 | Form: TABLET, FILM COATED
Manufacturer: Contract Pharmacal Corp.
Category: otc | Type: HUMAN OTC DRUG LABEL
Date: 20250908

ACTIVE INGREDIENTS: DOCUSATE SODIUM 50 mg/1 1; SENNOSIDES 8.6 mg/1 1
INACTIVE INGREDIENTS: FD&C YELLOW NO. 6; GUAR GUM; LECITHIN, SOYBEAN; MAGNESIUM STEARATE; MICROCRYSTALLINE CELLULOSE; POLYETHYLENE GLYCOL 4000; POLYVINYL ALCOHOL, UNSPECIFIED; TALC; SODIUM BENZOATE; TITANIUM DIOXIDE; STARCH, CORN; D&C YELLOW NO. 10 ALUMINUM LAKE; SILICON DIOXIDE

5609 - Export